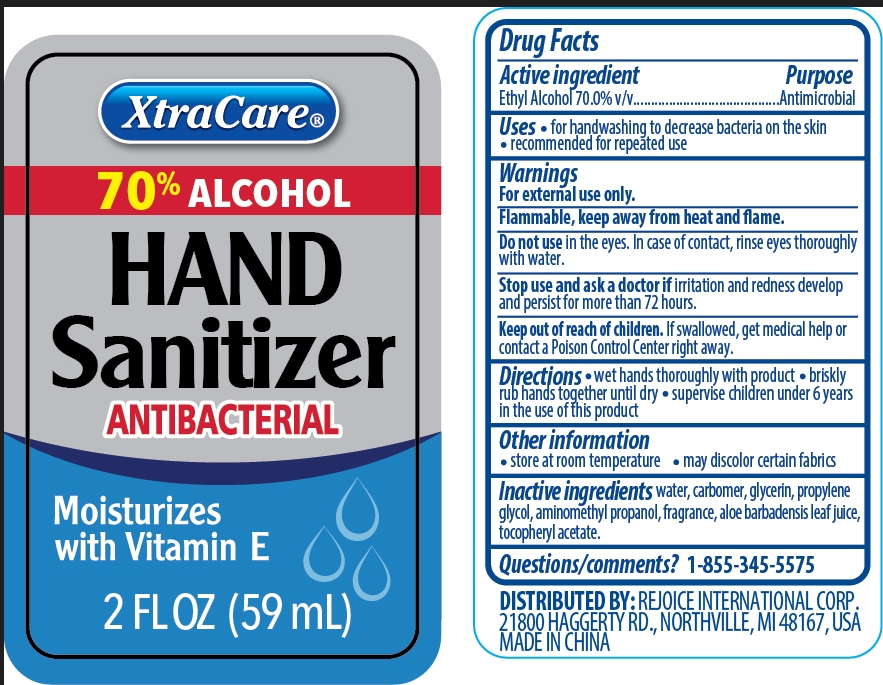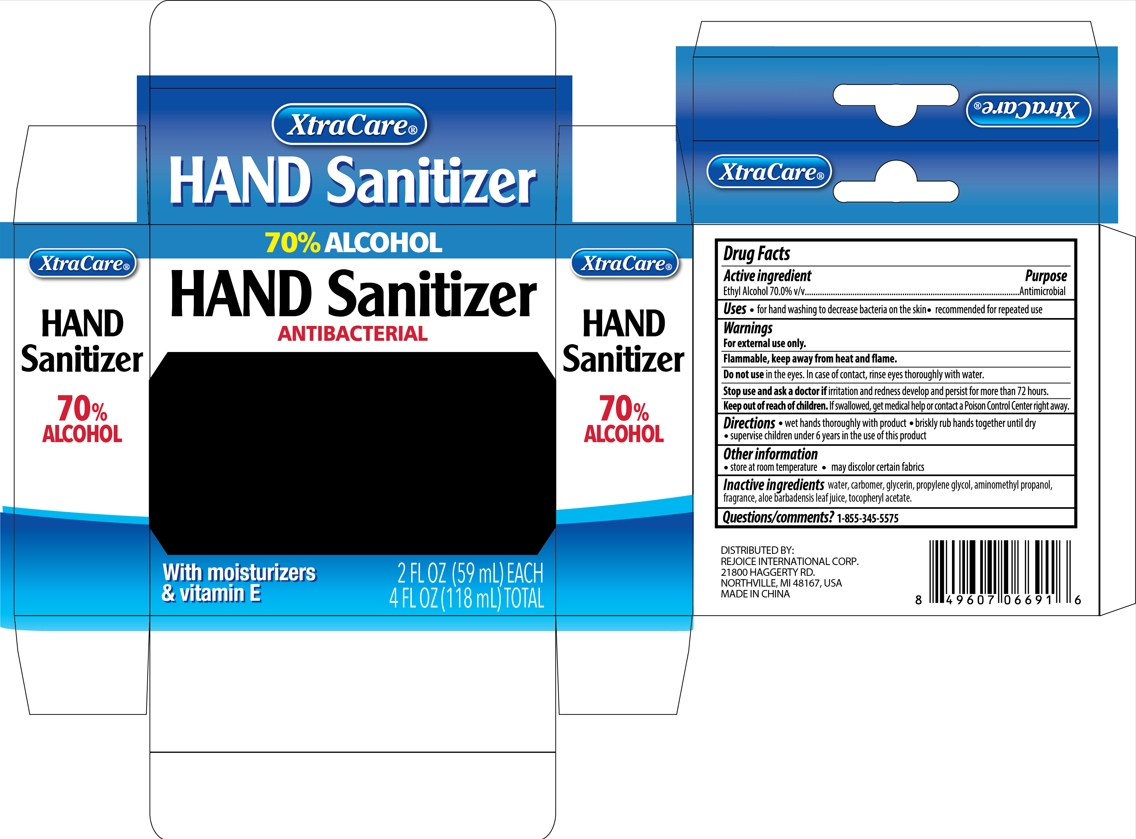 DRUG LABEL: Hand sanitizer 2oz 2pk original
NDC: 75742-027 | Form: GEL
Manufacturer: Zhejiang Guoyao Jingyue Aerosol Co., Ltd.
Category: otc | Type: HUMAN OTC DRUG LABEL
Date: 20231004

ACTIVE INGREDIENTS: ALCOHOL 70 mL/100 mL
INACTIVE INGREDIENTS: AMINOMETHYLPROPANOL; WATER; CARBOMER HOMOPOLYMER, UNSPECIFIED TYPE; GLYCERIN; PROPYLENE GLYCOL; .ALPHA.-TOCOPHEROL ACETATE; ALOE VERA LEAF

Active ingredient

Ethyl Alcohol 70.0%v/v

Purpose

Antimicrobial

Uses

For hand washing to decrease bacteria on the skin

Recommended for repeated use

Warnings

For external use only

Flammable, keep away from heat and flame.

Stop use and ask a doctor if irritation and redness develop and persist for more than 72 hours.

Keep out of reach of children

If swallowed, get medical help or contact a Poison Control Center right away.

Do not use in the eyes. In case of contact, rinse eyes thoroughly with water

Directions

wet hands thoroughly with product

Briskly rub hands together until dry

Supervise children under 6 years in the use of this product

Other information

Store at room temperature

May discolor certain fabrics

Inactive ingredients

water

carbomer

glycerin

propylene glycol

aminomethyl propanol

fragrance

aloe barbadensis leaf juice

tocopheryl acetate